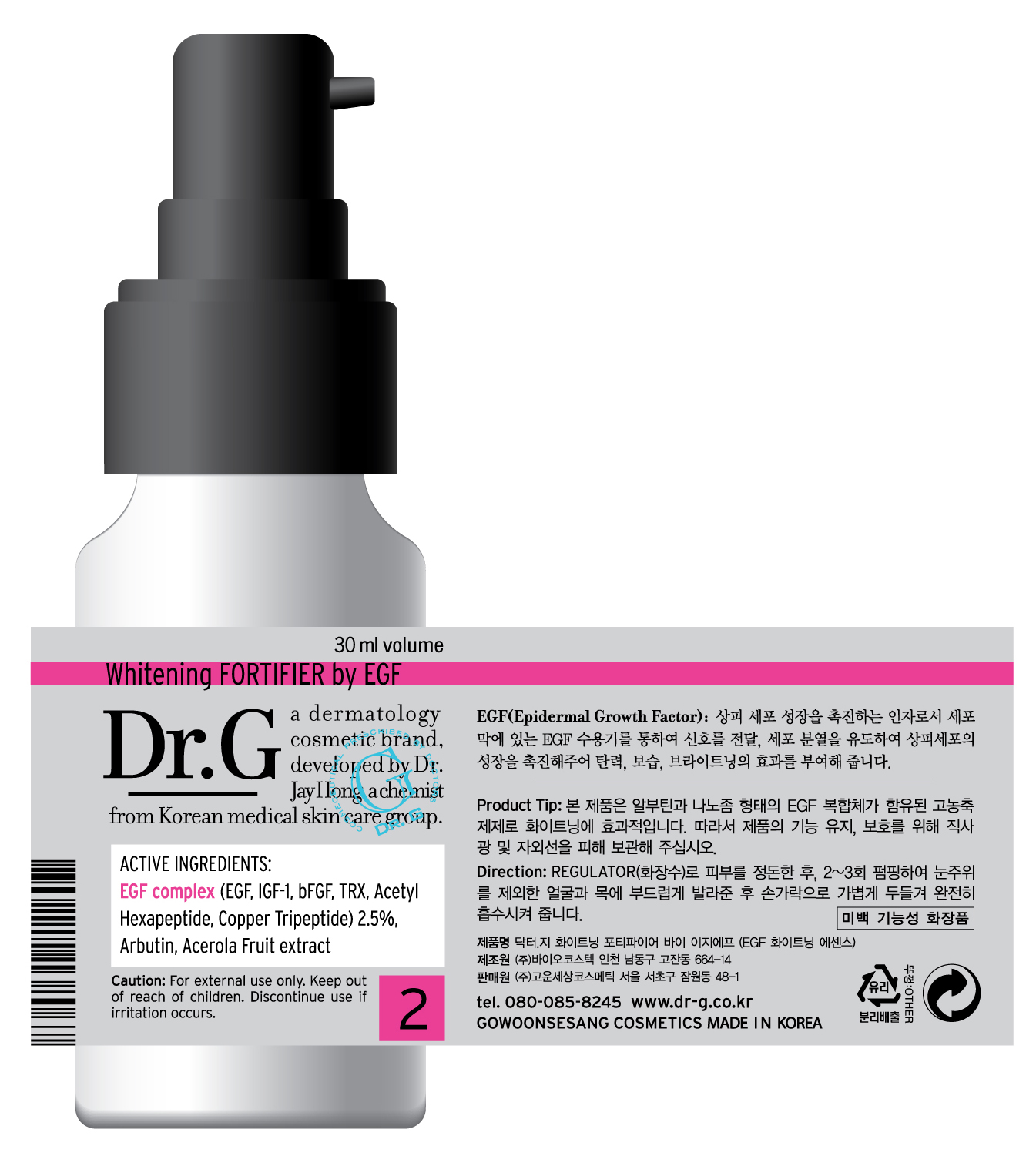 DRUG LABEL: Dr G Whitening FORTIFIER by EGF
NDC: 43948-4001 | Form: CREAM
Manufacturer: The Doctor's Cosmetic Inc
Category: otc | Type: HUMAN OTC DRUG LABEL
Date: 20091001

ACTIVE INGREDIENTS: ARBUTIN 0.6 mL/30 mL; GLYCERIN 3 mL/30 mL

ACTIVE INGREDIENTS:

Glycerin, EGF complex (EGF, IGF-1, bFGF, TRX, Acetyl Hexapeptide, Copper Tripeptide) 2.5%, Arbutin, Acerola Fruit extract

KEEP OUT OF REACH OF CHILDREN

Caution: For external use only. Keep out of reach of children. Discontinue use if irritation occurs.

WHEN USING

DIRECTION OF USE:

After conditioning skin with Regulator(toner) pump the essence 2 to 3 times and smoothly spread on face and neck. Avoid the eye area. Gently tap the skin with fingers for complete absorption.

PACKAGE LABEL

Label2c